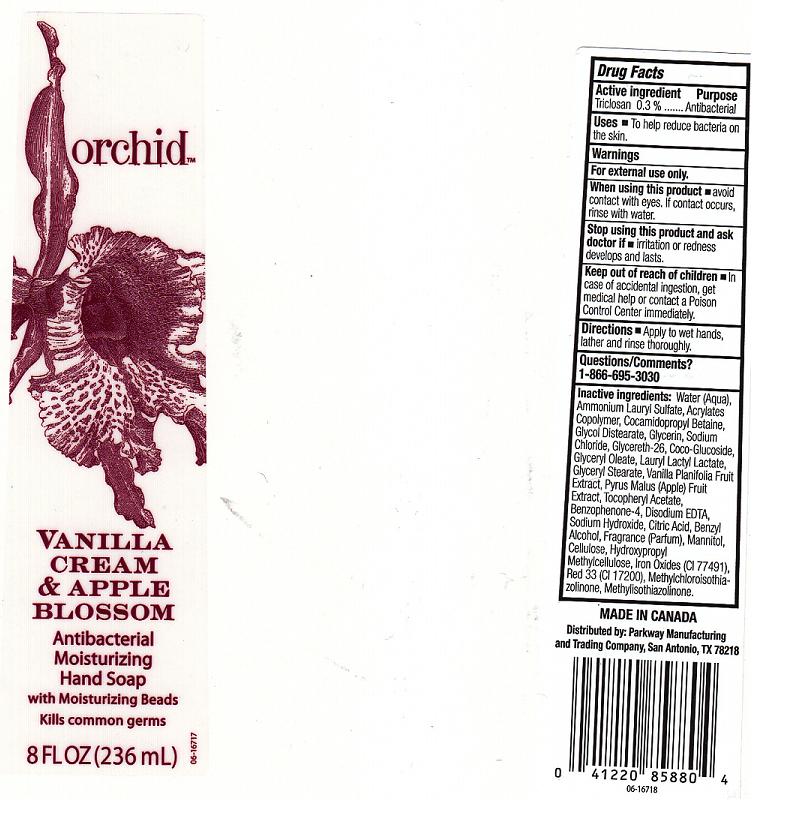 DRUG LABEL: VANILLA CREAM AND APPLE BLOSSOM ANTIBACTERIAL MOISTURIZING HAND SP
NDC: 37808-289 | Form: LIQUID
Manufacturer: HEB
Category: otc | Type: HUMAN OTC DRUG LABEL
Date: 20101223

ACTIVE INGREDIENTS: TRICLOSAN 0.3 mL/100 mL
INACTIVE INGREDIENTS: WATER; AMMONIUM LAURYL SULFATE; CARBOMER COPOLYMER TYPE A; COCAMIDOPROPYL BETAINE; GLYCOL DISTEARATE; GLYCERIN; SODIUM CHLORIDE; GLYCERETH-26; COCO GLUCOSIDE; GLYCERYL MONOOLEATE; LAURYL LACTATE; GLYCERYL MONOSTEARATE; VANILLA; APPLE; .ALPHA.-TOCOPHEROL ACETATE, D-; SULISOBENZONE; EDETATE DISODIUM; SODIUM HYDROXIDE; ANHYDROUS CITRIC ACID; BENZYL ALCOHOL; MANNITOL; POWDERED CELLULOSE; HYPROMELLOSES; FERRIC OXIDE RED; D&C RED NO. 33; METHYLCHLOROISOTHIAZOLINONE; METHYLISOTHIAZOLINONE

DRUG FACTS

ACTIVE INGREDIENT

TRICLOSAN 0.3 PERCENT

PURPOSE

ANTIBACTERIAL

WARNINGS

FOR EXTERNAL USE ONLY.

WHEN USING THIS PRODUCT

AVOID CONTACT WITH EYES. IF CONTACT OCCURS, RINSE WITH WATER.

STOP USING THIS PRODUCT AND ASK DOCTOR IF

IRRITATION OR REDNESS DEVELOPS OR LASTS.

KEEP OUT OF REACH OF CHILDREN

IN CASE OF ACCIDENTAL INGESTION, GET MEDICAL HELP OR CONTACT A POISON CONTROL CENTER IMMEDIATELY.

DIRECTIONS

APPLY TO WET HANDS, LATHER AND RINSE THOROUGHLY.

QUESTIONS OR COMMENTS

1-866-695-3030

INACTIVE INGREDIENTS

WATER, AMMONIUM LAURYL SULFATE, ACRYLATES COPOLYMER, COCAMIDOPROPYL BETAINE, GLYCOL DISTEARATE, GLYCERIN, SODIUM CHLORIDE, GYCERETH-26, COCO-GLUCOSIDE, GLYCERYL OLEATE, LAURYL LACTYL LACTATE, GLYCERYL STERATE, VANILLA PLANIFOLIA FRUIT EXTRACT, PYRUS MALUS (APPLE) FRUIT EXTRACT, TOCOPHERYL ACETATE, BENZOPHENONE-4, DISODIUM EDTA, SODIUM HYDROXIDE, CITRIC ACID, BENZYL ALCOHOL, FRAGRANCE, MANNITOL, CELLULOSE, HYDROXYPROPYL METHYLCELLULOSE, IRON OXIDES (CI 77491), RED 33 (CI 17200), METHYLCHLOROISOTHIAZOLINONE, METHYLISOTHIAZOLINONE.

USES

To help reduce bacteria on the skin.